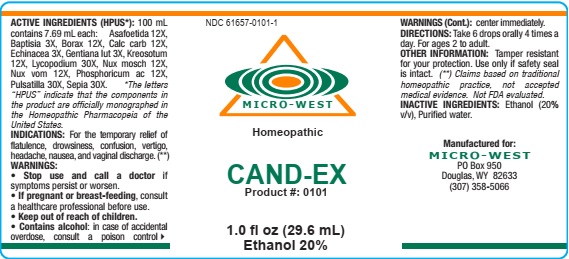 DRUG LABEL: CAND-EX
NDC: 61657-0101 | Form: LIQUID
Manufacturer: WHITE MANUFACTURING INC. DBA MICRO WEST
Category: homeopathic | Type: HUMAN OTC DRUG LABEL
Date: 20210121

ACTIVE INGREDIENTS: LYCOPODIUM CLAVATUM SPORE 30 [hp_X]/30 mL; STRYCHNOS NUX-VOMICA SEED 12 [hp_X]/30 mL; ECHINACEA, UNSPECIFIED 3 [hp_X]/30 mL; BAPTISIA TINCTORIA 3 [hp_X]/30 mL; PULSATILLA VULGARIS 30 [hp_X]/30 mL; SEPIA OFFICINALIS JUICE 30 [hp_X]/30 mL; PHOSPHORIC ACID 12 [hp_X]/30 mL; WOOD CREOSOTE 12 [hp_X]/30 mL; OYSTER SHELL CALCIUM CARBONATE, CRUDE 12 [hp_X]/30 mL; SODIUM BORATE 12 [hp_X]/30 mL; GENTIANA LUTEA ROOT 3 [hp_X]/30 mL; NUTMEG 12 [hp_X]/30 mL; ASAFETIDA 12 [hp_X]/30 mL
INACTIVE INGREDIENTS: ALCOHOL

DRUG FACTS

ACTIVE INGREDIENTS

Asafoetida 12X

Baptisia 3X

Borax 12X

Calc carb 12X

Echinacea 3X

Gentiana lut 3X

Kreosotum 12X

Lycopodium 30X

Nux mosch 12X

Nux vom 12X

Phosphoricum ac 12X

Pulsatilla 30X

Sepia 30X

Inactive ingredients

Inactive ingredients: Alcohol (20% v/v), Purified water

PURPOSE

FOR THE TEMPORARY RELIEF OF FLATULENCE, DROWSINESS, CONFUSION, VERITGO, HEADACHE, NAUSEA, AND VAGINAL DISCHARGE

KEEP OUT OF REACH OF CHILDREN

INDICATIONS

INDICATIONS: FOR THE TEMPORARY RELIEF OF FLATULENCE, DROWSINESS, CONFUSION, VERITGO, HEADACHE, NAUSEA, AND VAGINAL DISCHARGE

WARNING

WARNINGS: Stop use and call a doctor if symptoms persist or worsen. If pregnant or breast-feeding, consult a healthcare professional before use. Contains alcohol; in case of accidental overdose, consult a poison control center immediately.

DIRECTIONS

DIRECTIONS:Take 6 drops orally, 4 times a day. For ages 2 to adult

Other Information

Other information: Tamper resistant for your protection. Use only if safety seal is intact

MANUFACTURE

MANUFACTURED FOR:

MICRO WEST

P.O. Box 950

DOUGLAS, WY 82633
1-307-358-5066

LABEL

NDC 61657-0101-1

MICRO-WEST

Homeopathic

CAND-EX

Product #: 0101

1.0 fl oz (29.6 mL)

Ethanol 20%